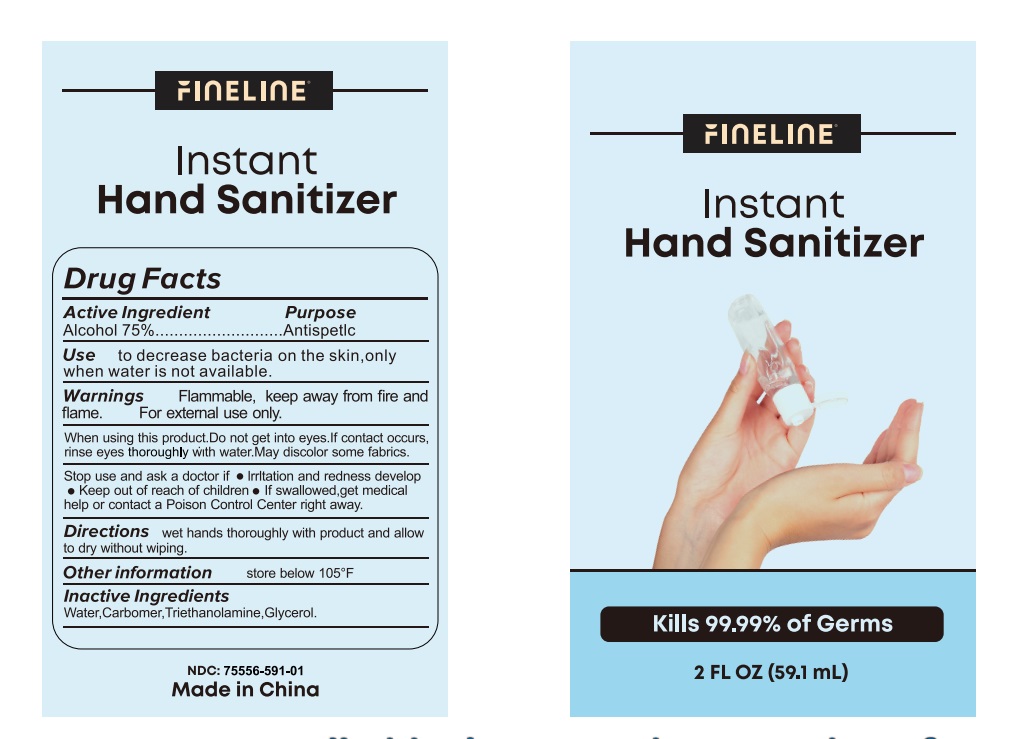 DRUG LABEL: Instant Hand Sanitizer
NDC: 75556-591 | Form: GEL
Manufacturer: ZHEJIANG SHUNAN INDUSTRY&TRADE CO.,LTD
Category: otc | Type: HUMAN OTC DRUG LABEL
Date: 20200817

ACTIVE INGREDIENTS: ALCOHOL 44.325 mL/59.1 mL
INACTIVE INGREDIENTS: CARBOMER HOMOPOLYMER, UNSPECIFIED TYPE; GLYCERIN; WATER; TROLAMINE

75556-591 59.1 ml SHUNAN

This is a hand sanitizer manufactured according to the Temporary Policy for Preparation of Certain Alcohol-Based Hand Sanitizer Products During the Public Health Emergency (CoViD-19); Guidance for Industry.

The hand sanitizer is manufactured using only the following United States Pharmacopoeia (USP) grade ingredients in the preparation of the product (percentage in final product formulation) consistent with World Health Organization (WHO) recommendations:

1. Alcohol (ethanol) (USP or Food Chemical Codex (FCC) grade) (80%, volume/volume (v/v)) in an aqueous solution denatured according to Alcohol and Tobacco Tax and Trade Bureau regulations in 27 CFR part 20.
2. Glycerol (1.45% v/v).
3. Hydrogen peroxide (0.125% v/v).
4. Sterile distilled water or boiled cold water.

The firm does not add other active or inactive ingredients. Different or additional ingredients may impact the quality and potency of the product.

Active Ingredient(s)

Alcohol 75% v/v. Purpose: Antiseptic

Purpose

Antiseptic, Hand Sanitizer

Use

to decrease bacteria on the skin, only when water is not available.

Warnings

- Flammable. Keep away from fire and flame.
- For external use only.

Do not use

- in children less than 2 months of age
- on open skin wounds

When using this product . Do not get into eyes. If contact occurs, rinse eyes thoroughly with water. May discolor some fabrics.

Stop use and ask a doctor if

- Irritation or redness develop
- Keep out of reach of children
- If swallowed. get medical help or contact a Poison Control Center right away.

Keep out of reach of children. If swallowed, get medical help or contact a Poison Control Center immediately.

Directions

- wet hands thoroughly with product and allow to dry without wiping.

Other information

- Store below 105℉

Inactive ingredients

Water,Carbomer, Triethanolamine, Glycerol

Package Label - Principal Display Panel

59.1 mL in 1 Bottle NDC: 75556-591-01